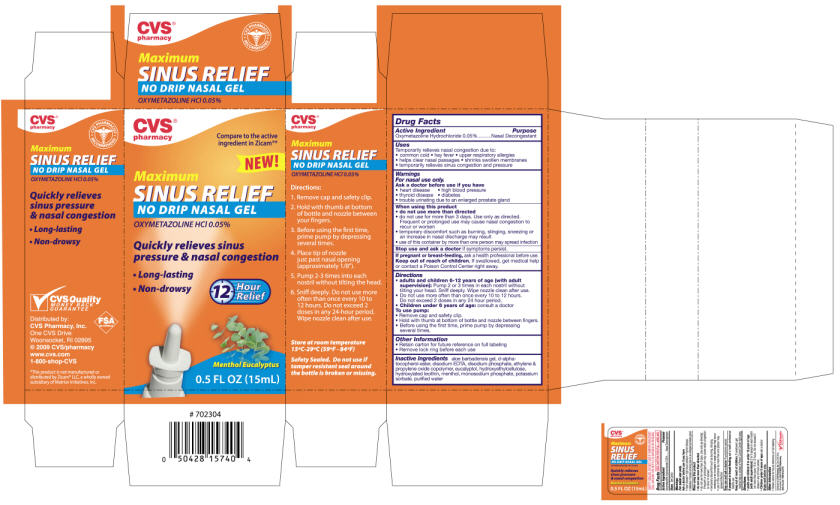 DRUG LABEL: Oxymetazoline Hydrochloride
NDC: 64762-864 | Form: SPRAY, METERED
Manufacturer: Dynamic Pharmaceuticals
Category: otc | Type: HUMAN OTC DRUG LABEL
Date: 20091230

ACTIVE INGREDIENTS: Oxymetazoline Hydrochloride 0.2 mg/0.4 mL

CVS®
pharmacy

Drug Facts

Active Ingredient

Oxymetazoline Hydrochloride 0.05%

Purpose

Nasal Decongestant

Uses

Temporarily relieves nasal congestion due to:

- common cold
- hay fever
- upper respiratory allergies
- helps clear nasal passages
- shrinks swollen membranes
- temporarily relieves sinus congestion and pressure

Warnings

For nasal use only.

Ask a doctor before use if you have

- heart disease
- high blood pressure
- thyroid disease
- diabetes
- trouble urinating due to an enlarged prostate gland

When using this product

- do not use more than directed
- do not use for more than 3 days. Use only as directed.
  Frequent or prolonged use may cause nasal congestion to recur or worsen
- temporary discomfort such as burning, stinging, sneezing or an increase in nasal discharge may result
- use of this container by more than one person may spread infection

Stop use and ask a doctor if symptoms persist.

PREGNANCY OR BREAST FEEDING

If pregnant or breast-feeding, ask a health professional before use.

Keep out of reach of children, If swallowed, get medical help or contact a Poison Control Center right away.

Directions

- adults and children 6-12 years of age (with adult supervision): Pump 2 or 3 times in each nostril without tilting your head. Sniff deeply. Wipe nozzle clean after use.
- Do not use more often than once every 10 to 12 hours.
- Do not exceed 2 doses in any 24 hour period.
- Children under 6 years of age: consult a doctor

To use pump:

- Remove cap and safety clip.
- Hold with thumb at bottom of bottle and nozzle between fingers.
- Before using the first time, prime pump by depressing several times.

Other Information

- Retain carton for future reference on full labeling
- Remove lock ring before each use

Inactive Ingredients

aloe barbadensis gel, d-alpha-tocopherol-ester, disodium EDTA, disodium phosphate, ethylene & propylene oxide copolymer, eucalyptol, hydroxyethylcellulose, hydroxylated lecithin, menthol, monosodium phosphate, potassium sorbate, purified water

Distributed by:
CVS Pharmacy, Inc.
One CVS Drive
Woonsocket, RI 02895

PRINCIPAL DISPLAY PANEL - 15 mL Carton

CVS®
pharmacy

Compare to the active
ingredient in Zicam®*

NEW!

Maximum
SINUS RELIEF
NO DRIP NASAL GEL
OXYMETAZOLINE HCl 0.05%

Quickly relieves sinus
pressure & nasal congestion

- Long-lasting
- Non-drowsy

12
Hour
Relief

Menthol Eucalyptus

0.5 FL OZ (15mL)